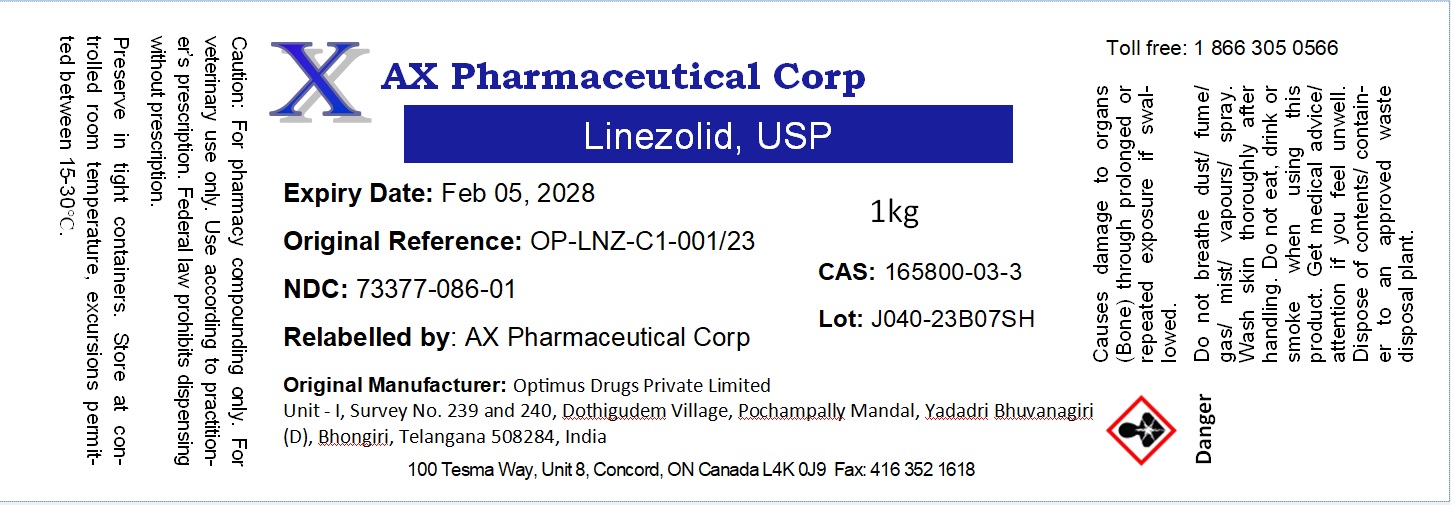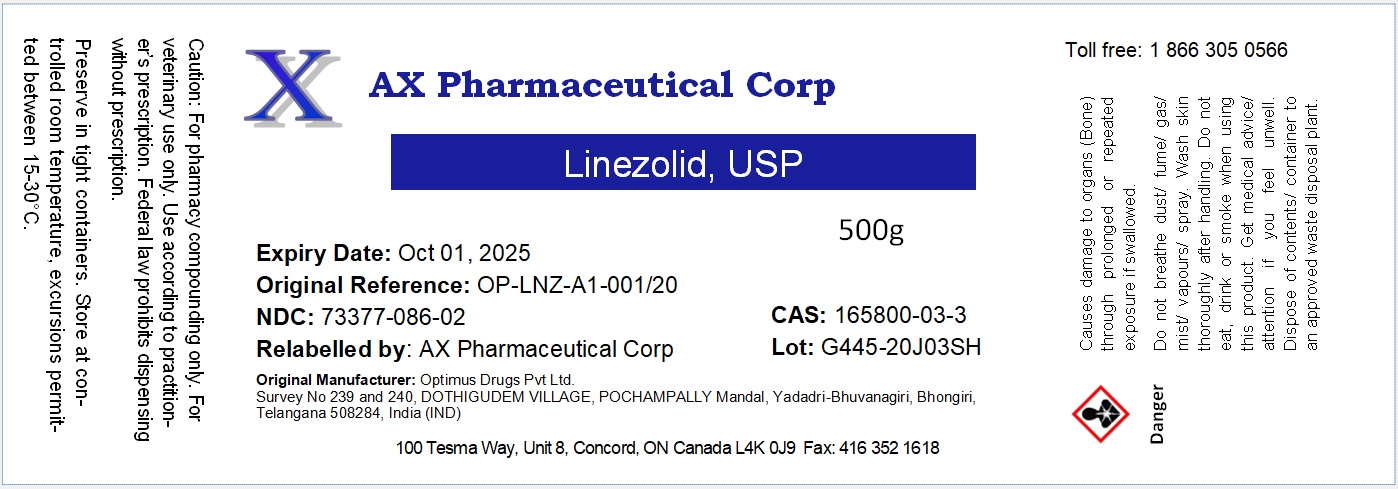 DRUG LABEL: Linezolid
NDC: 73377-086 | Form: POWDER
Manufacturer: AX Pharmaceutical Corp
Category: other | Type: BULK INGREDIENT - ANIMAL DRUG
Date: 20241022

ACTIVE INGREDIENTS: LINEZOLID 1 kg/1 kg

Linezolid